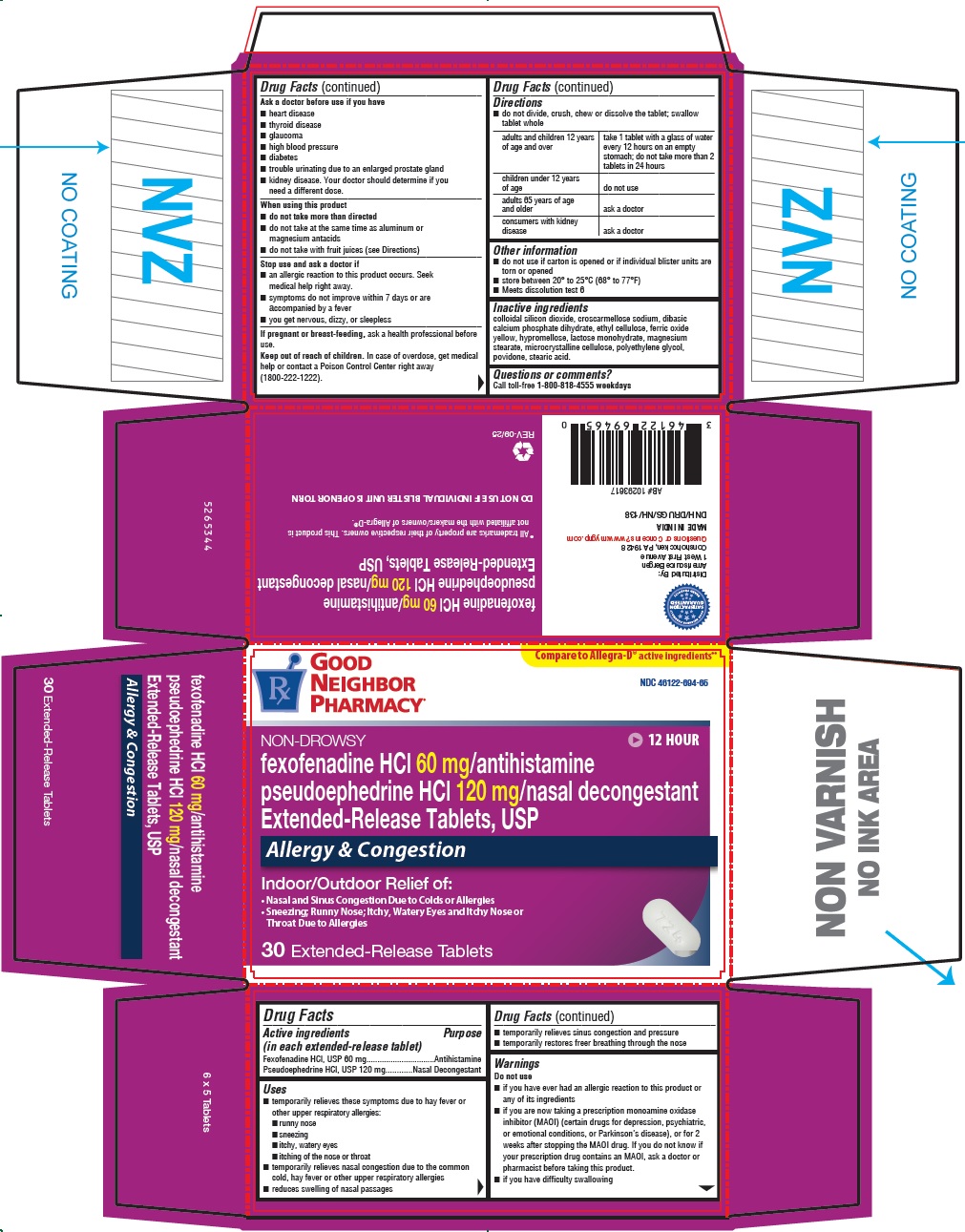 DRUG LABEL: Fexofenadine Hydrochloride and Pseudoephedrine Hydrochloride

NDC: 46122-694 | Form: TABLET, FILM COATED, EXTENDED RELEASE
Manufacturer: AmeriSource Bergen
Category: otc | Type: HUMAN OTC DRUG LABEL
Date: 20251114

ACTIVE INGREDIENTS: FEXOFENADINE HYDROCHLORIDE 60 mg/1 1; PSEUDOEPHEDRINE HYDROCHLORIDE 120 mg/1 1
INACTIVE INGREDIENTS: LACTOSE MONOHYDRATE; MICROCRYSTALLINE CELLULOSE; CROSCARMELLOSE SODIUM; POVIDONE K30; MAGNESIUM STEARATE; DIBASIC CALCIUM PHOSPHATE DIHYDRATE; SILICON DIOXIDE; ETHYLCELLULOSE, UNSPECIFIED; FERRIC OXIDE YELLOW; STEARIC ACID; HYPROMELLOSE, UNSPECIFIED; POLYETHYLENE GLYCOL, UNSPECIFIED

Fexofenadine Hydrochloride and Pseudoephedrine Hydrochloride

Drug Facts

ACTIVE INGREDIENT

Active ingredients (in each extended-release tablet) | Purpose
Fexofenadine HCl, USP 60 mg | Antihistamine
Pseudoephedrine HCl, USP 120 mg | Nasal Decongestant

Uses

- temporarily relieves these symptoms due to hay fever or other upper respiratory allergies:
  - runny nose
  - sneezing
  - itchy, watery eyes
  - itching of the nose or throat
- temporarily relieves nasal congestion due to the common cold, hay fever or other upper respiratory allergies
- reduces swelling of nasal passages
- temporarily relieves sinus congestion and pressure
- temporarily restores freer breathing through the nose

Warnings

Do not use

- if you have ever had an allergic reaction to this product or any of its ingredients
- if you are now taking a prescription monoamine oxidase inhibitor (MAOI) (certain drugs for depression, psychiatric, or emotional conditions, or Parkinson's disease), or for 2 weeks after stopping the MAOI drug. If you do not know if your prescription drug contains an MAOI, ask a doctor or pharmacist before taking this product.
- if you have difficulty swallowing

Ask a doctor before use if you have

- heart disease
- thyroid disease
- glaucoma
- high blood pressure
- diabetes
- trouble urinating due to an enlarged prostate gland
- kidney disease. Your doctor should determine if you need a different dose.

When using this product

- do not take more than directed
- do not take at the same time as aluminum or magnesium antacids
- do not take with fruit juices (see Directions)

Stop use and ask a doctor if

- an allergic reaction to this product occurs. Seek medical help right away.
- symptoms do not improve within 7 days or are accompanied by a fever
- you get nervous, dizzy, or sleepless

PREGNANCY OR BREAST FEEDING

If pregnant or breast-feeding,ask a health professional before use.

Keep out of reach of children.In case of overdose, get medical help or contact a Poison Control Center right away (1800-222-1222).

Directions

- do not divide, crush, chew or dissolve the tablet; swallow tablet whole

adults and children 12 years of age and over | take 1 tablet with a glass of water every 12 hours on an empty stomach; do not take more than 2 tablets in 24 hours
children under 12 years of age | do not use
adults 65 years of age and older | ask a doctor
consumers with kidney disease | ask a doctor

Other information

- do not use if carton is opened or if individual blister units are torn or opened
- store between 20° to 25°C (68° to 77°F)
- Meets dissolution test 6

Inactive ingredients

colloidal silicon dioxide, croscarmellose sodium, dibasic calcium phosphate dihydrate, ethyl cellulose, ferric oxide yellow, hypromellose, lactose monohydrate, magnesium stearate, microcrystalline cellulose, polyethylene glycol, povidone, stearic acid.

Questions or comments?

Call toll-free 1-800-818-4555 weekdays

Distributed By:
AmerisourceBergen
1 West First Avenue
Conshohocken, PA 19428

PRINCIPAL DISPLAY PANEL - 30 Tablet Blister Pack Carton

Compare to Allegra-D®active ingredients**

GOOD
NEIGHBOR
PHARMACY®

NDC 46122-694-65

NON-DROWSY

12 HOUR

fexofenadine HCl 60 mg/antihistamine
pseudoephedrine HCl 120 mg/nasal decongestant
Extended-Release Tablets, USP

Indoor & Outdoor Allergies

Allergy & Congestion

Indoor/Outdoor Relief of:

- Nasal and Sinus Congestion Due to Colds or Allergies
- Sneezing; Runny Nose; Itchy, Watery Eyes and Itchy Nose or
  Throat Due to Allergies

30 Extended-Release Tablets